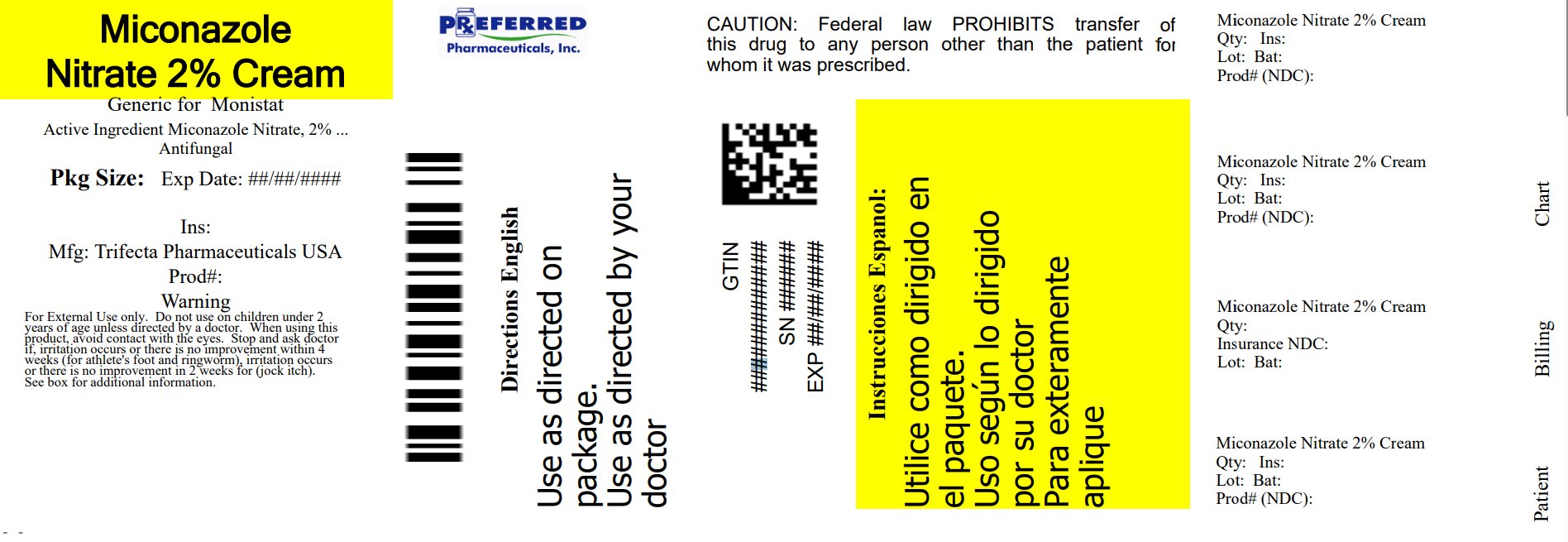 DRUG LABEL: MICONAZOLE Nitrate 2% Cream ANTIFUNGAL
NDC: 68788-8845 | Form: CREAM
Manufacturer: Preferred Pharmaceuticals Inc.
Category: otc | Type: HUMAN OTC DRUG LABEL
Date: 20250324

ACTIVE INGREDIENTS: MICONAZOLE NITRATE 2 g/100 g
INACTIVE INGREDIENTS: CARBOMER HOMOPOLYMER, UNSPECIFIED TYPE; CETOSTEARYL ALCOHOL; DIMETHYL SULFOXIDE; EDETATE DISODIUM; ETHYLPARABEN; GLYCERIN; GLYCERYL DISTEARATE; MINERAL OIL; POLYOXYL 20 CETOSTEARYL ETHER; WATER; STEARIC ACID; TROLAMINE; PETROLATUM

MICONAZOLE Nitrate 2% Cream ANTIFUNGAL

Active ingredient

Miconazole Nitrate 2%

Purpose

Anti-Fungal

Keep out of reach of children. If swallowed, get medical help or contact a Poison Control Center immediately.

Uses

- proven clinically effective in the treatment of most athlete's foot (tinea pedis), jock itch (tinea crurus), and ringworm (tinea capitis)
- relieves itching, scaling, cracking, burning and discomfort associated with these conditions.

Warnings

For external use only. Do not use if the safety-sealed tube is punctured or damaged.

Do not use on children under 2 years of age unless directed by a healthcare professional. When using this product avoid contact with the eyes.

Stop use and ask a healthcare professional if • irritation occurs or if there is no improvement within 4 weeks (for athlete's foot and ringworm) • Irritation occurs, or if there is no improvement within 2 weeks (for jock itch).

Directions

Clean the affected area and dry thoroughly • Apply a thin layer of the product over affected area twice daily (morning and night) or as directed by a healthcare professional • Supervise children in the use of this product.

For athlete's foot: • Use daily for 4 weeks. If condition persists, consult a healthcare professional. • Pay special attention to the spaces between the toes • Wear well fitting, ventilated shoes • Change socks atleast once daily.

For ringworm: Use daily for 4 weeks. If condition persists, consult a healthcare professional.

For jock itch: Use daily for 2 weeks. If condition persists longer, consult a healthcare professional.

This product is not effective on the scalp or nails.

INACTIVE INGREDIENT

Inactive ingredients Carbomer, cetostearyl alcohol, dimethyl sulfoxide, edetate disodium, ethylparaben, glycerol, glyceryl distearate, mineral oil, peregal-o, purified water, stearic acid, triethanolamine, petrolatum.

Other Information

• Store at 15° - 30° c (59° - 86° f) • Lot number and expiration date see crimp of tube or see box. • To open: Unscrew cap, tear safety seal off.

You may report serious side effects to: QC@trifecta-pharma.com

FAST RELIEF 100% GUARANTEED

Relieves Itching and Burning

Also Cures Athlete's Foot and Ringworm

Distributed by:
Trifecta Pharmaceuticals USA TM
101 NE Third Avenue Suite 1500
Ft. Lauderdale, FL 33301 USA
www.trifecta-pharma.com

Relabeled By: Preferred Pharmaceuticals Inc.

68788-8845-3